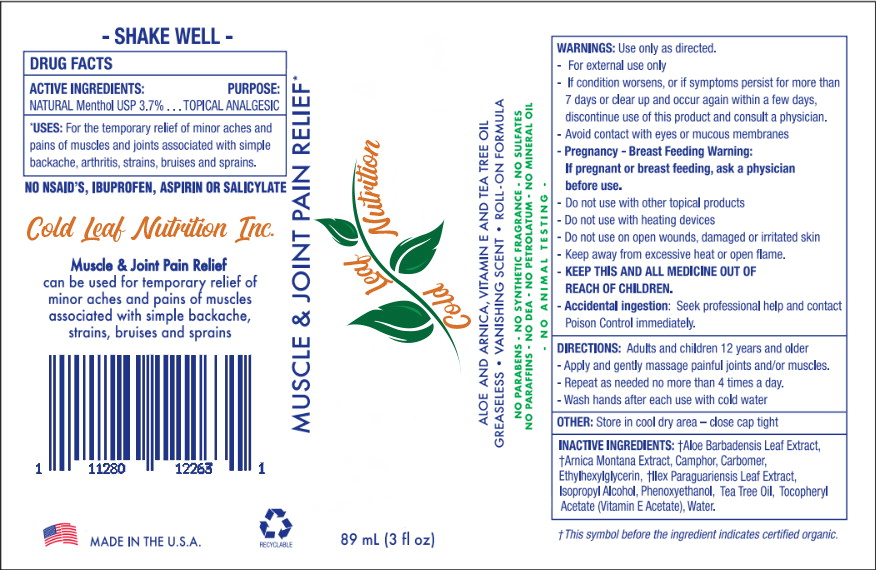 DRUG LABEL: COLD LEAF NUTRITION MUSCLE AND JOINT PAIN RELIEF
NDC: 66902-114 | Form: GEL
Manufacturer: NATURAL ESSENTIALS, INC.
Category: otc | Type: HUMAN OTC DRUG LABEL
Date: 20180927

ACTIVE INGREDIENTS: MENTHOL 37 mg/1 mL
INACTIVE INGREDIENTS: ALOE VERA LEAF; ARNICA MONTANA; CAMPHOR (SYNTHETIC); CARBOMER HOMOPOLYMER TYPE C (ALLYL PENTAERYTHRITOL CROSSLINKED); ILEX PARAGUARIENSIS LEAF; ISOPROPYL ALCOHOL; PHENOXYETHANOL; TEA TREE OIL; .ALPHA.-TOCOPHEROL ACETATE; WATER

Cold Leaf Nutrition Inc.
DRUG FACTS

ACTIVE INGREDIENTS

NATURAL Menthol USP 3.7%

PURPOSE:

TOPICAL ANALGESIC

*USES:

For the temporary relief of minor aches and pains of muscles and joints associated with simple backache, arthritis, strains, bruises and sprains.

WARNINGS:

Use only as directed.

- For external use only
- If condition worsens, or if symptoms persist for more than 7 days or clear up and occur again within a few days, discontinue use of this product and consult a physician.
- Avoid contact with eyes or mucous membranes

- Pregnancy - Breast Feeding Warning:
- If pregnant or breast feeding, ask a physician before use.

- Do not use with other topical products
- Do not use with heating devices
- Do not use on open wounds, damaged or irritated skin
- Keep away from excessive heat or open flame.

KEEP OUT OF REACH OF CHILDREN

- KEEP THIS AND ALL MEDICINE OUT OF REACH OF CHILDREN.
- Accidental ingestion: Seek professional help and contact Poison Control immediately.

DIRECTIONS:

Adults and children 12 years and older

- Apply and gently massage painful joints and/or muscles.
- Repeat as needed no more than 4 times a day.
- Wash hands after each use with cold water

OTHER:

Store in cool dry area - close cap tight

INACTIVE INGREDIENTS:

†Aloe Barbadensis Leaf Extract, †Arnica Montana Extract, Camphor, Carbomer, Ethylhexylglycerin, †llex Paraguariensis Leaf Extract, Isopropyl Alcohol, Phenoxyethanol, Tea Tree Oil, Tocopheryl Acetate (Vitamin E Acetate), Water.

†This symbol before the ingredient indicates certified organic:

Principal Display Panel - Cold Leaf Nutrition Container Label

MUSCLE & JOINT PAIN RELIEF*

Leaf Cold Nutrition

ALOE AND ARNICA, VITAMIN E AND TEA TREE OIL
GREASELESS • VANISHING SCENT • ROLL ON FORMULA

NO PARABENS • NO SYNTHETIC FRAGRANCE • NO SULFATES
NO PARAFFINS • NO DEA • NO PETROLATUM • NO MINERAL OIL
• NO ANIMAL TESTING

89 mL (3 fl oz)